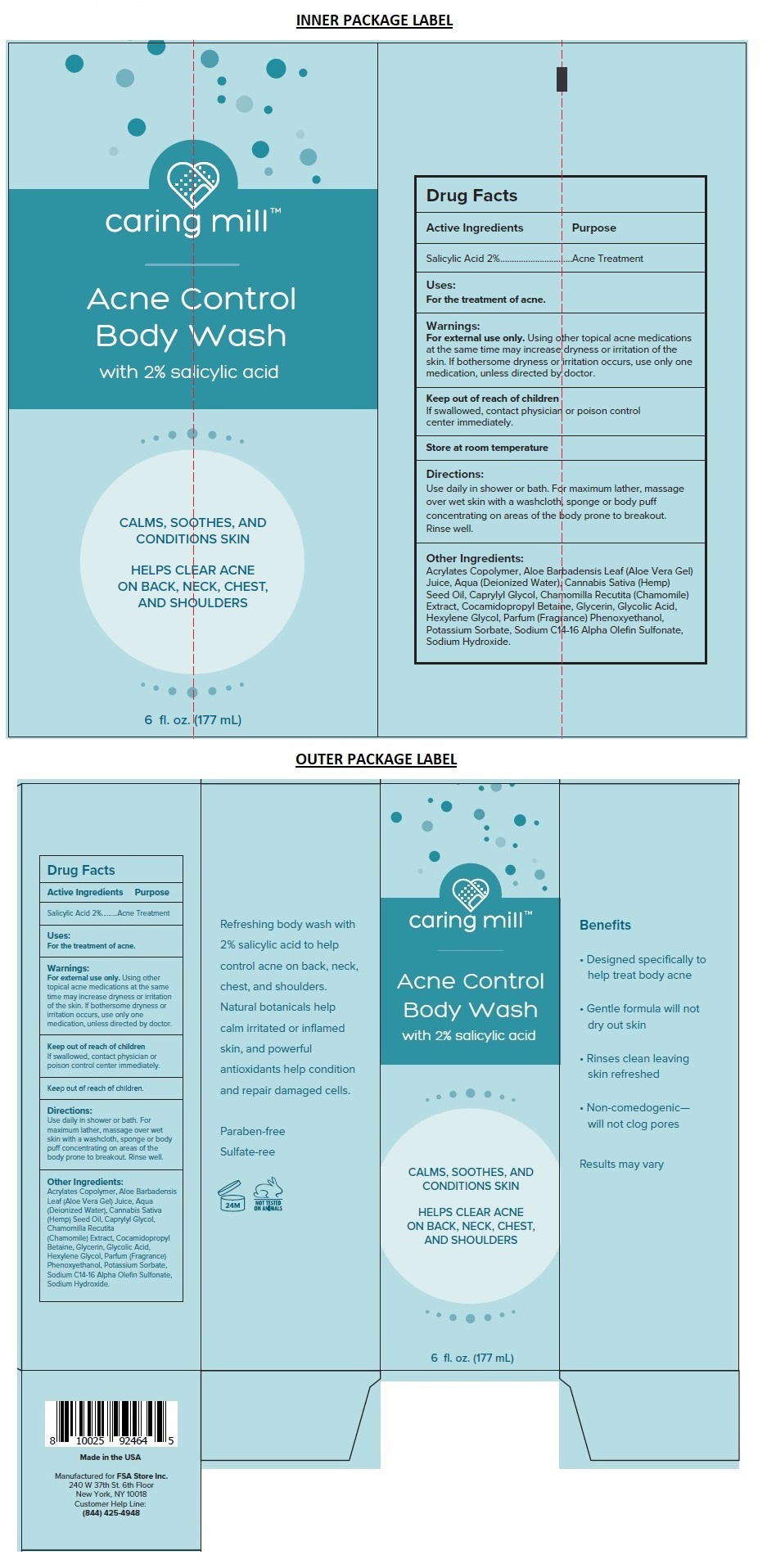 DRUG LABEL: caring mill Acne Control Body Wash
NDC: 71328-061 | Form: GEL
Manufacturer: Clixit, Llc
Category: otc | Type: HUMAN OTC DRUG LABEL
Date: 20210621

ACTIVE INGREDIENTS: SALICYLIC ACID 20 mg/1 mL
INACTIVE INGREDIENTS: METHACRYLIC ACID AND ETHYL ACRYLATE COPOLYMER; ALOE VERA LEAF; WATER; CANNABIS SATIVA SEED OIL; CAPRYLYL GLYCOL; CHAMOMILE; COCAMIDOPROPYL BETAINE; GLYCERIN; GLYCOLIC ACID; HEXYLENE GLYCOL; PHENOXYETHANOL; POTASSIUM SORBATE; SODIUM C14-16 OLEFIN SULFONATE; SODIUM HYDROXIDE

caring mill™ Acne Control Body Wash

Active Ingredients

Salicylic Acid 2%

Purpose

Acne Treatment

Uses:

For the treatment of acne

Warnings:

For external use only. Using other topical acne medications at the same time may increase dryness or irritation of the skin. If bothersome dryness or irritation occurs, use only one medication, unless directed by doctor.

Keep out of reach of children.
If swallowed, get medical help or call a Poison Control Center right away.

Directions:

Use daily in shower or bath. For maximum lather, massage over wet skin with a washcloth, sponge or body puff concentrating on areas of the body prone to breakout. Rinse well.

Other Ingredients:

Acrylates Copolymer, Aloe Barbadensis Leaf (Aloe Vera Gel) Juice, Aqua (Deionized Water), Cannabis Sativa (Hemp) Seed Oil, Caprylyl Glycol, Chamomilla Recutita (Chamomile) Extract, Cocamidopropyl Betaine, Glycerin, Glycolic Acid, Hexylene Glycol, Parfum (Fragrance), Phenoxyethanol, Potassium Sorbate, Sodium C14-16 Alpha Olefin Sulfonate, Sodium Hydroxide.

STORAGE AND HANDLING

Store at room temperature

CALMS, SOOTHES, AND CONDITIONS SKIN

HELPS CLEAR ACNE ON BACK, NECK, CHEST AND SHOULDERS

Benefits

• Designed specifically to help treat body acne

• Gentle formula will not dry out skin

• Rinses clean leaving skin refreshed

• Non-comedogenic— will not clog pores

Results may vary

Refreshing body wash with 2% salicylic acid to help control acne on back, neck, chest, and shoulders. Natural botanicals help calm irritated or inflamed skin, and powerful antioxidants help condition and repair damaged cells.

Paraben-free

Sulfate-free

NOT TESTED ON ANIMALS

Made in the USA

Manufactured for FSA Store Inc.
240 W 37th St. 6th Floor
New York, NY 10018
Customer Help Line:
(844) 425-4948